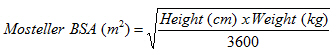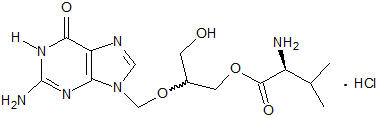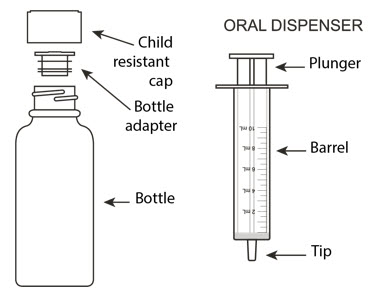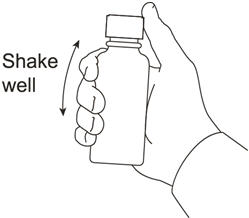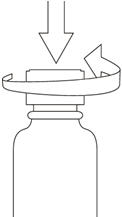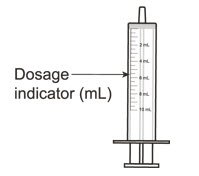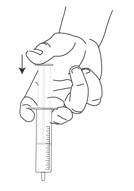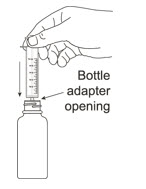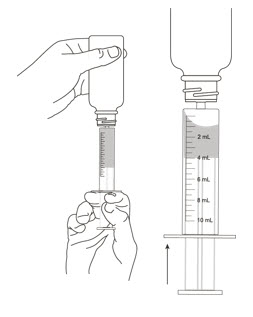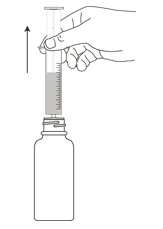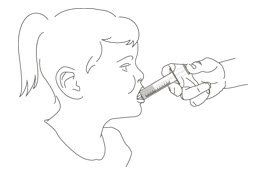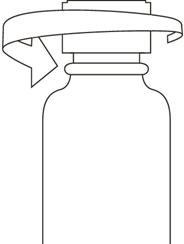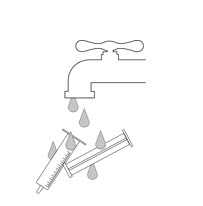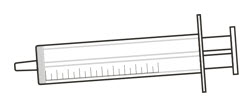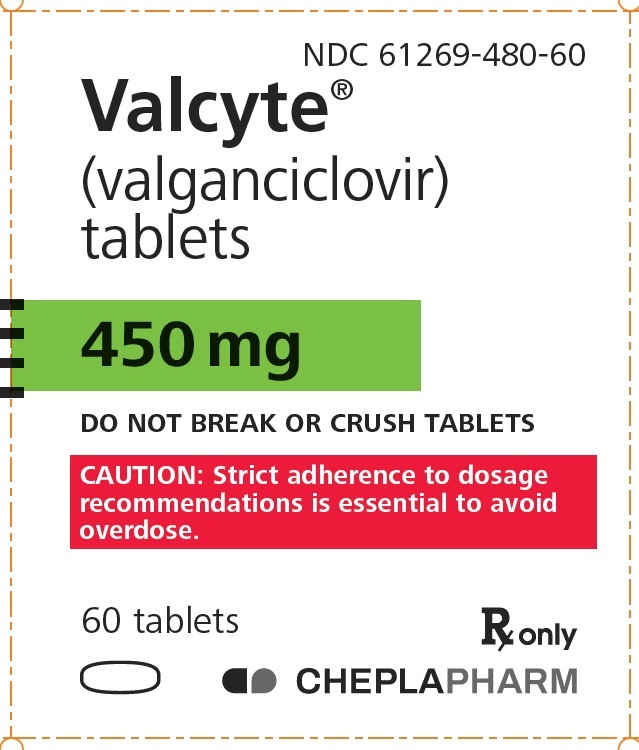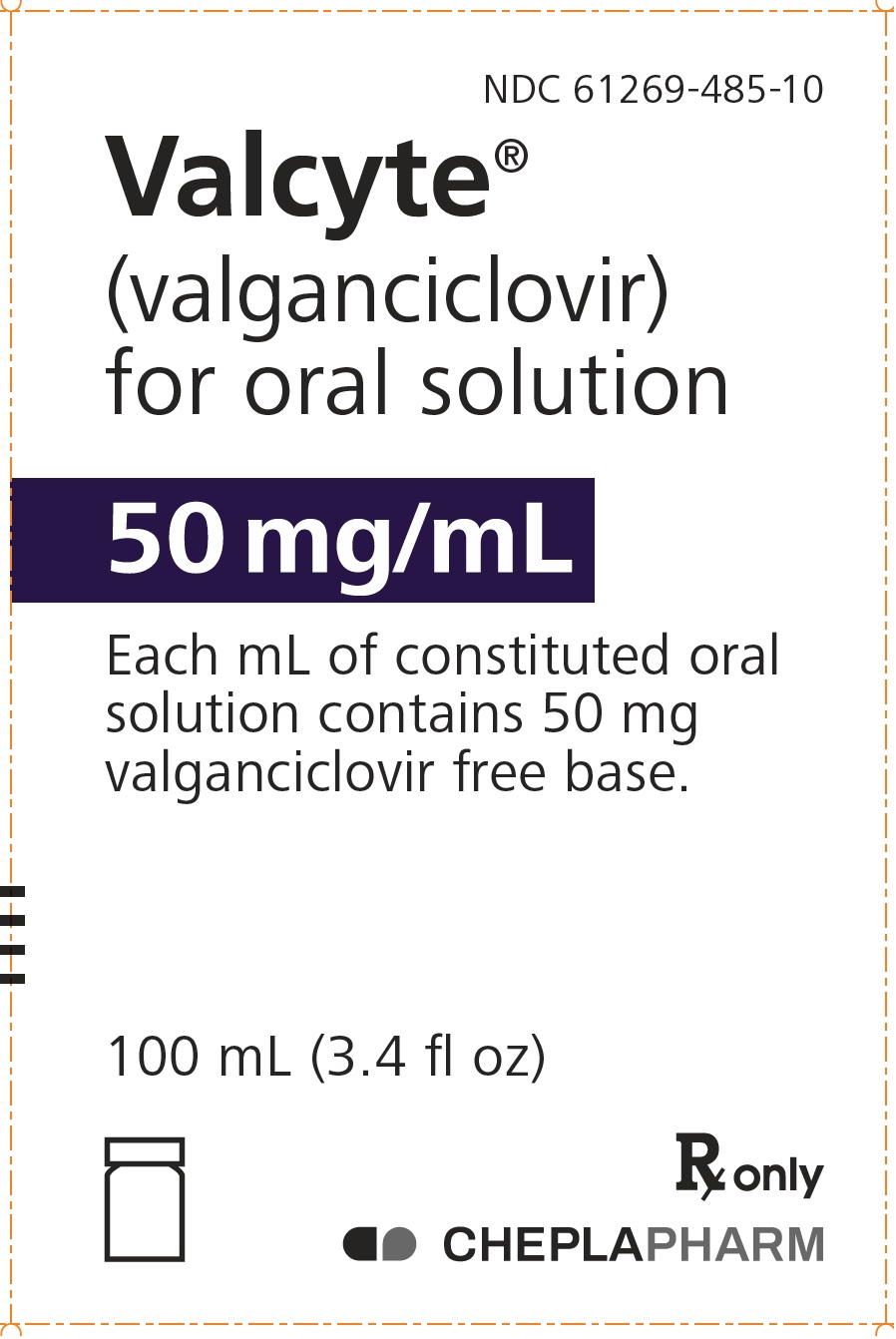 DRUG LABEL: Valcyte
NDC: 61269-480 | Form: TABLET, FILM COATED
Manufacturer: H2-Pharma, LLC
Category: prescription | Type: HUMAN PRESCRIPTION DRUG LABEL
Date: 20251208

ACTIVE INGREDIENTS: VALGANCICLOVIR HYDROCHLORIDE 450 mg/1 1
INACTIVE INGREDIENTS: MICROCRYSTALLINE CELLULOSE; POVIDONE K30; CROSPOVIDONE (120 .MU.M); STEARIC ACID; HYPROMELLOSE 2910 (6 MPA.S); TITANIUM DIOXIDE; POLYETHYLENE GLYCOL 400; FERRIC OXIDE RED; POLYSORBATE 80

HIGHLIGHTS OF PRESCRIBING INFORMATION

These highlights do not include all the information needed to use VALCYTE® safely and effectively. See full prescribing information for VALCYTE.
VALCYTE (valganciclovir) tablets, for oral use
VALCYTE (valganciclovir) for oral solution
Initial U.S. Approval: 2001

WARNING: HEMATOLOGIC TOXICITY, IMPAIRMENT OF FERTILITY, FETAL TOXICITY, MUTAGENESIS AND CARCINOGENESIS

See full prescribing information for complete boxed warning.

- Hematologic Toxicity: Severe leukopenia, neutropenia, anemia, thrombocytopenia, pancytopenia, and bone marrow failure including aplastic anemia have been reported in patients treated with VALCYTE. (5.1)
- Impairment of Fertility: Based on animal data and limited human data, VALCYTE may cause temporary or permanent inhibition of spermatogenesis in males and suppression of fertility in females. (5.3)
- Fetal Toxicity: Based on animal data, VALCYTE has the potential to cause birth defects in humans. (5.4)
- Mutagenesis and Carcinogenesis: Based on animal data, VALCYTE has the potential to cause cancers in humans. (5.5)

1 INDICATIONS AND USAGE

VALCYTE is a deoxynucleoside analogue cytomegalovirus (CMV) DNA polymerase inhibitor indicated for:

Adult Patients (1.1)

- Treatment of CMV retinitis in patients with acquired immunodeficiency syndrome (AIDS).
- Prevention of CMV disease in kidney, heart, and kidney-pancreas transplant patients at high risk.

Pediatric Patients (1.2)

- Prevention of CMV disease in kidney and heart transplant patients at high risk.

2 DOSAGE AND ADMINISTRATION

Adult Dosage (2.2)
Treatment of CMV retinitis | Induction: 900 mg (two 450 mg tablets) twice a day for 21 days Maintenance: 900 mg (two 450 mg tablets) once a day
Prevention of CMV disease in heart or kidney-pancreas transplant patients | 900 mg (two 450 mg tablets) once a day within 10 days of transplantation until 100 days post-transplantation
Prevention of CMV disease in kidney transplant patients | 900 mg (two 450 mg tablets) once a day within 10 days of transplantation until 200 days post-transplantation
Pediatric Dosage (2.3)
Prevention of CMV disease in kidney transplant patients 4 months to 16 years of age | Dose once a day within 10 days of transplantation until 200 days post-transplantation according to dosage algorithm (note the calculation of creatinine clearance using a modified Schwartz formula in children)
Prevention of CMV disease in heart transplant patients 1 month to 16 years of age | Dose once a day within 10 days of transplantation until 100 days post-transplantation according to dosage algorithm (note the calculation of creatinine clearance using a modified Schwartz formula in children)

- VALCYTE for oral solution and tablets should be taken with food. (2.1, 12.3)
- VALCYTE tablets should not be broken or crushed. (2.6)
- Adult patients should use VALCYTE tablets, not VALCYTE for oral solution. (2.1)
- Adults with renal impairment: Adjust dose based on creatinine clearance. For adult patients receiving hemodialysis a dose recommendation cannot be given. (2.5, 8.6, 12.3)

3 DOSAGE FORMS AND STRENGTHS

- Tablets: 450 mg. (3)
- Oral Solution: 50 mg per mL. (3)

4 CONTRAINDICATIONS

Hypersensitivity to valganciclovir or ganciclovir. (4)

5 WARNINGS AND PRECAUTIONS

- Acute renal failure: Acute renal failure may occur in elderly patients (with or without reduced renal function), patients who receive concomitant nephrotoxic drugs, or inadequately hydrated patients. Use with caution in elderly patients or those taking nephrotoxic drugs, reduce dosage in patients with renal impairment, and monitor renal function. (2.5, 5.2, 8.5, 8.6)

6 ADVERSE REACTIONS

- Adult patients: Most common adverse reactions and laboratory abnormalities (reported in at least one indication by greater than or equal to 20% of patients) are diarrhea, pyrexia, fatigue, nausea, tremor, neutropenia, anemia, leukopenia, thrombocytopenia, headache, insomnia, urinary tract infection, and vomiting. (6.1)
- Pediatric patients: Most common adverse reactions and laboratory abnormalities (reported in greater than or equal to 20% of pediatric solid organ transplant recipients) are diarrhea, pyrexia, upper respiratory tract infection, urinary tract infection, vomiting, neutropenia, leukopenia, and headache. (6.1)

To report SUSPECTED ADVERSE REACTIONS, contact 1-866-946-3684 or FDA at 1-800-FDA-1088 or www.fda.gov/medwatch.

7 DRUG INTERACTIONS

- Imipenem-cilastatin: Seizures were reported in patients receiving ganciclovir and imipenem-cilastatin. Concomitant use is not recommended unless the potential benefits outweigh the risks. (7)
- Cyclosporine or amphotericin B: When coadministered with valganciclovir, the risk of nephrotoxicity may be increased. Monitor renal function. (5.2, 7)
- Mycophenolate mofetil (MMF): When coadministered with valganciclovir, the risk of hematological and renal toxicity may be increased. Monitor for ganciclovir and MMF toxicity. (7)
- Other drugs associated with myelosuppression or nephrotoxicity: Due to potential for increased toxicity, consider for concomitant use with valganciclovir only if the potential benefits are judged to outweigh the risks. (7)
- Didanosine: Ganciclovir coadministered with didanosine may increase didanosine levels. Monitor for didanosine toxicity (e.g., pancreatitis). (7)
- Probenecid: May increase ganciclovir levels. Monitor for evidence of ganciclovir toxicity. (7)

8 USE IN SPECIFIC POPULATIONS

- Lactation: Breastfeeding is not recommended with use of VALCYTE. (8.2)

FULL PRESCRIBING INFORMATION

WARNING: HEMATOLOGIC TOXICITY, IMPAIRMENT OF FERTILITY, FETAL TOXICITY, MUTAGENESIS AND CARCINOGENESIS

- Hematologic Toxicity: Severe leukopenia, neutropenia, anemia, thrombocytopenia, pancytopenia, and bone marrow failure including aplastic anemia have been reported in patients treated with VALCYTE [see Warnings and Precautions (5.1)].
- Impairment of Fertility: Based on animal data and limited human data, VALCYTE may cause temporary or permanent inhibition of spermatogenesis in males and suppression of fertility in females [see Warnings and Precautions (5.3)].
- Fetal Toxicity: Based on animal data, VALCYTE has the potential to cause birth defects in humans [see Warnings and Precautions (5.4)].
- Mutagenesis and Carcinogenesis: Based on animal data, VALCYTE has the potential to cause cancers in humans [see Warnings and Precautions (5.5)].

1 INDICATIONS AND USAGE

1.1 Adult Patients

Treatment of Cytomegalovirus (CMV) Retinitis: VALCYTE is indicated for the treatment of CMV retinitis in patients with acquired immunodeficiency syndrome (AIDS) [see Clinical Studies (14.1)].

Prevention of CMV Disease: VALCYTE is indicated for the prevention of CMV disease in kidney, heart, and kidney-pancreas transplant patients at high risk (Donor CMV seropositive/Recipient CMV seronegative [D+/R-]) [see Clinical Studies (14.1)].

1.2 Pediatric Patients

Prevention of CMV Disease: VALCYTE is indicated for the prevention of CMV disease in kidney transplant patients (4 months to 16 years of age) and heart transplant patients (1 month to 16 years of age) at high risk [see Clinical Studies (14.2)].

2 DOSAGE AND ADMINISTRATION

2.1 General Dosing Information

- Adult patients should use VALCYTE tablets, not VALCYTE for oral solution.
- VALCYTE for oral solution and tablets should be taken with food [see Clinical Pharmacology (12.3)].
- VALCYTE for oral solution (50 mg/mL) must be prepared by the pharmacist prior to dispensing to the patient [see Dosage and Administration (2.4)].

2.2 Recommended Dosage in Adult Patients with Normal Renal Function

For dosage recommendations in adult patients with renal impairment [see Dosage and Administration (2.5)].

Treatment of CMV Retinitis:

- Induction: The recommended dosage is 900 mg (two 450 mg tablets) taken orally twice a day for 21 days.
- Maintenance: Following induction treatment, or in adult patients with inactive CMV retinitis, the recommended dosage is 900 mg (two 450 mg tablets) taken orally once a day.

Prevention of CMV Disease:

- For adult patients who have received a heart or kidney-pancreas transplant, the recommended dosage is 900 mg (two 450 mg tablets) taken orally once a day starting within 10 days of transplantation until 100 days post-transplantation.
- For adult patients who have received a kidney transplant, the recommended dosage is 900 mg (two 450 mg tablets) taken orally once a day starting within 10 days of transplantation until 200 days post-transplantation.

2.3 Recommended Dosage in Pediatric Patients

Prevention of CMV Disease in Pediatric Kidney Transplant Patients: For pediatric kidney transplant patients 4 months to 16 years of age, the recommended once daily mg dose (7 × BSA × CrCl) should start within 10 days of post-transplantation until 200 days post-transplantation.

Prevention of CMV Disease in Pediatric Heart Transplant Patients: For pediatric heart transplant patients 1 month to 16 years of age, the recommended once daily mg dose (7 × BSA × CrCl) should start within 10 days of transplantation until 100 days post-transplantation.

The recommended once daily dosage of VALCYTE is based on body surface area (BSA) and creatinine clearance (CrCl) derived from a modified Schwartz formula, and is calculated using the equation below:

Pediatric Dose (mg) = 7 × BSA × CrCl (calculated using a modified Schwartz formula). If the calculated Schwartz creatinine clearance exceeds 150 mL/min/1.73m^2, then a maximum value of 150 mL/min/1.73m^2 should be used in the equation. The k values used in the modified Schwartz formula are based on pediatric patient age, as shown in Table 1.

Schwartz Creatinine Clearance (mL / min / 1.73m^2) =

k × Height (cm)

Serum Creatinine (mg / dL)

Table 1 k Values According to Pediatric Patient Age *
k value | Pediatric Patient Age
0.33 | Infants less than 1 year of age with low birth weight for gestational age
0.45 | Infants less than 1 year of age with birth weight appropriate for gestational age
0.45 | Children aged 1 to less than 2 years
0.55 | Boys aged 2 to less than 13 years Girls aged 2 to less than 16 years
0.7 | Boys aged 13 to 16 years

Monitor serum creatinine levels regularly and consider changes in height and body weight and adapt the dose as appropriate during prophylaxis period.

All calculated doses should be rounded to the nearest 25 mg increment for the actual deliverable dose. The oral dispenser is graduated in 0.5 mL increments. A 50 mg dose is equivalent to 1 mL. If the calculated dose exceeds 900 mg, a maximum dose of 900 mg should be administered. VALCYTE for oral solution is the preferred formulation since it provides the ability to administer a dose calculated according to the formula above; however, VALCYTE tablets may be used if the calculated doses are within 10% of available tablet strength (450 mg). For example, if the calculated dose is between 405 mg and 495 mg, one 450 mg tablet may be taken. Before prescribing VALCYTE tablets, pediatric patients should be assessed for the ability to swallow tablets.

2.4 Preparation of VALCYTE for Oral Solution

Wearing disposable gloves is recommended during reconstitution and when wiping the outer surface of the bottle/cap and the table after reconstitution. Prior to dispensing to the patient, VALCYTE for oral solution must be prepared by the pharmacist as follows [see How Supplied/Storage and Handling (16)]:

- Measure 91 mL of purified water in a graduated cylinder.
- Shake the VALCYTE bottle to loosen the powder. Remove the child resistant bottle cap and add approximately half the total amount of water for constitution to the bottle and shake the closed bottle well for about 1 minute. Add the remainder of water and shake the closed bottle well for about 1 minute. This prepared solution contains 50 mg of valganciclovir free base per 1 mL.
- Remove the child resistant bottle cap and push the bottle adapter into the neck of the bottle.
- Close bottle with child resistant bottle cap tightly. This will assure the proper seating of the bottle adapter in the bottle and child resistant status of the cap.
- Store constituted oral solution under refrigeration at 2°C to 8°C (36°F to 46°F) for no longer than 49 days. Do not freeze.
- Write the discard date of the constituted oral solution on the bottle label.

The patient package insert, which includes the dosing instructions for patients, and 2 oral dispensers should be dispensed to the patient [see Patient Counseling Information (17)].

2.5 Dosage Recommendation for Adult Patients with Renal Impairment

Serum creatinine levels or estimated creatinine clearance should be monitored regularly during treatment. Dosage recommendations for adult patients with reduced renal function are provided in Table 2. For adult patients on hemodialysis (CrCl less than 10 mL/min), a dose recommendation for VALCYTE cannot be given [see Use in Specific Populations (8.5, 8.6), Clinical Pharmacology (12.3)].

Table 2 Dosage Recommendations for Adult Patients with Impaired Renal Function
VALCYTE 450 mg Tablets
CrCl* (mL/min) | Induction Dose | Maintenance/Prevention Dose
≥ 60 | 900 mg twice daily | 900 mg once daily
40 – 59 | 450 mg twice daily | 450 mg once daily
25 – 39 | 450 mg once daily | 450 mg every 2 days
10 – 24 | 450 mg every 2 days | 450 mg twice weekly
< 10 (on hemodialysis) | not recommended | not recommended

*An estimated creatinine clearance in adults is calculated from serum creatinine by the following formulas:

For males = | (140 – age [years]) × (body weight [kg])
For males = | (72) × (serum creatinine [mg/dL])

For females = 0.85 × male value

Dosing in pediatric patients with renal impairment can be done using the recommended equations because CrCl is a component in the calculation [see Dosage and Administration (2.3)].

2.6 Handling and Disposal

Caution should be exercised in the handling of VALCYTE tablets and VALCYTE for oral solution. Tablets should not be broken or crushed. Because valganciclovir is considered a potential teratogen and carcinogen in humans, caution should be observed in handling broken tablets, the powder for oral solution, and the constituted oral solution [see Warnings and Precautions (5.4, 5.5)]. Avoid direct contact with broken or crushed tablets, the powder for oral solution, and the constituted oral solution with skin or mucous membranes. If such contact occurs, wash thoroughly with soap and water, and rinse eyes thoroughly with plain water.

Handle and dispose VALCYTE according to guidelines for antineoplastic drugs because ganciclovir shares some of the properties of antitumor agents (i.e., carcinogenicity and mutagenicity).^2

3 DOSAGE FORMS AND STRENGTHS

- VALCYTE tablets: 450 mg, pink, film-coated convex oval tablets with "VGC" on one side and "450" on the other side.
- VALCYTE for oral solution: 50 mg per mL, supplied as a white to slightly yellow powder for constitution, forming a colorless to brownish yellow tutti-frutti flavored solution. Available in glass bottles containing approximately 100 mL of solution after constitution.

4 CONTRAINDICATIONS

VALCYTE is contraindicated in patients who have had a demonstrated clinically significant hypersensitivity reaction (e.g., anaphylaxis) to valganciclovir, ganciclovir, or any component of the formulation [see Adverse Reactions (6.1)].

5 WARNINGS AND PRECAUTIONS

5.1 Hematologic Toxicity

Severe leukopenia, neutropenia, anemia, thrombocytopenia, pancytopenia, and bone marrow failure including aplastic anemia have been reported in patients treated with VALCYTE or ganciclovir. VALCYTE should be avoided if the absolute neutrophil count is less than 500 cells/µL, the platelet count is less than 25,000/µL, or the hemoglobin is less than 8 g/dL. VALCYTE should also be used with caution in patients with pre-existing cytopenias and in patients receiving myelosuppressive drugs or irradiation. Cytopenia may occur at any time during treatment and may worsen with continued dosing. Cell counts usually begin to recover within 3 to 7 days after discontinuing drug. In patients with severe leukopenia, neutropenia, anemia and/or thrombocytopenia, treatment with hematopoietic growth factors may be considered.

Due to the frequency of neutropenia, anemia, and thrombocytopenia in patients receiving VALCYTE [see Adverse Reactions (6.1)], complete blood counts with differential and platelet counts should be performed frequently, especially in infants, in patients with renal impairment, and in patients in whom ganciclovir or other nucleoside analogues have previously resulted in leukopenia, or in whom neutrophil counts are less than 1000 cells/µL at the beginning of treatment. Increased monitoring for cytopenias may be warranted if therapy with oral ganciclovir is changed to VALCYTE because of increased plasma concentrations of ganciclovir after VALCYTE administration [see Clinical Pharmacology (12.3)].

5.2 Acute Renal Failure

Acute renal failure may occur in:

- Elderly patients with or without reduced renal function. Caution should be exercised when administering VALCYTE to geriatric patients, and dosage reduction is recommended for those with impaired renal function [see Dosage and Administration (2.5), Use in Specific Populations (8.5, 8.6)].
- Patients receiving potential nephrotoxic drugs. Caution should be exercised when administering VALCYTE to patients receiving potential nephrotoxic drugs.
- Patients without adequate hydration. Adequate hydration should be maintained for all patients.

5.3 Impairment of Fertility

Based on animal data and limited human data, VALCYTE at the recommended human doses may cause temporary or permanent inhibition of spermatogenesis in males, and may cause suppression of fertility in females. Advise patients that fertility may be impaired with use of VALCYTE [see Use in Specific Populations (8.1, 8.3), Nonclinical Toxicology (13.1)].

5.4 Fetal Toxicity

Ganciclovir may cause fetal toxicity when administered to pregnant women based on findings in animal studies. When given to pregnant rabbits at dosages resulting in 2 times the human exposure (based on AUC), ganciclovir caused malformations in multiple organs of the fetuses. Maternal and fetal toxicity were also observed in pregnant mice and rabbits. Therefore, VALCYTE has the potential to cause birth defects. Pregnancy should be avoided in female patients taking VALCYTE and in females with male partners taking VALCYTE. Females of reproductive potential should be advised to use effective contraception during treatment and for at least 30 days following treatment with VALCYTE because of the potential risk to the fetus. Similarly, males should be advised to use condoms during and for at least 90 days following treatment with VALCYTE [see Dosage and Administration (2.6), Use in Specific Populations (8.1, 8.3), Nonclinical Toxicology (13.1)].

5.5 Mutagenesis and Carcinogenesis

Animal data indicate that ganciclovir is mutagenic and carcinogenic. VALCYTE should therefore be considered a potential carcinogen in humans [see Dosage and Administration (2.6), Nonclinical Toxicology (13.1)].

6 ADVERSE REACTIONS

The following serious adverse reactions are discussed in greater detail in other sections of the labeling:

- Hematologic Toxicity [see Warnings and Precautions (5.1)].
- Acute Renal Failure [see Warnings and Precautions (5.2)].
- Impairment of Fertility [see Warnings and Precautions (5.3)].
- Fetal Toxicity [see Warnings and Precautions (5.4)].
- Mutagenesis and Carcinogenesis [see Warnings and Precautions (5.5)].

The most common adverse reactions and laboratory abnormalities reported in at least one indication by greater than or equal to 20% of adult patients treated with VALCYTE tablets are diarrhea, pyrexia, fatigue, nausea, tremor, neutropenia, anemia, leukopenia, thrombocytopenia, headache, insomnia, urinary tract infection, and vomiting. The most common reported adverse reactions and laboratory abnormalities reported in greater than or equal to 20% of pediatric solid organ transplant recipients treated with VALCYTE for oral solution or tablets are diarrhea, pyrexia, upper respiratory tract infection, urinary tract infection, vomiting, neutropenia, leukopenia, and headache.

6.1 Clinical Trials Experience

Because clinical trials are conducted under widely varying conditions, adverse reaction rates observed in the clinical trials of a drug cannot be directly compared to rates in the clinical trials of another drug and may not reflect rates observed in practice.

Valganciclovir, a prodrug of ganciclovir, is rapidly converted to ganciclovir after oral administration. Adverse reactions known to be associated with ganciclovir usage can therefore be expected to occur with VALCYTE.

Adverse Reactions in Adults:

Treatment of CMV Retinitis in AIDS Patients: In a clinical study for the treatment of CMV retinitis in HIV-infected patients, the adverse reactions reported by patients receiving VALCYTE tablets (n=79) or intravenous ganciclovir (n=79) for 28 days of randomized therapy (21 days induction dose and 7 days maintenance dose), respectively, included diarrhea (16%, 10%), nausea (8%, 14%), and headache (9%, 5%). The incidence of adverse reactions was similar between the group who received VALCYTE tablets and the group who received intravenous ganciclovir. The frequencies of neutropenia (ANC less than 500/µL) were 11% for patients receiving VALCYTE tablets compared with 13% for patients receiving intravenous ganciclovir. Anemia (Hgb less than 8 g/dL) occurred in 8% of patients in each group. Other laboratory abnormalities occurred with similar frequencies in the two groups.

Adverse reactions and laboratory abnormalities are available for 370 patients who received maintenance therapy with VALCYTE tablets 900 mg once daily in two open-label clinical trials. Approximately 252 (68%) of these patients received VALCYTE tablets for more than nine months (maximum duration was 36 months). Table 3 and Table 4 show pooled selected adverse reactions and abnormal laboratory values from these patients.

Table 3 Pooled Selected Adverse Reactions Reported in greater than or equal to 5% of Patients who Received VALCYTE Tablets Maintenance Therapy for CMV Retinitis
 | Patients with CMV Retinitis
Adverse Reactions according to Body System | VALCYTE Tablets (N=370) %
Gastrointestinal system
Diarrhea | 41
Nausea | 30
Vomiting | 21
Abdominal pain | 15
General disorders and administrative site conditions
Pyrexia | 31
Nervous system disorders
Headache | 22
Insomnia | 16
Neuropathy peripheral | 9
Paresthesia | 8
Eye disorders
Retinal detachment | 15

Table 4 Pooled Selected Laboratory Abnormalities Reported in Patients Who Received VALCYTE Tablets Maintenance Therapy for the Treatment of CMV Retinitis
 | Patients with CMV Retinitis
Laboratory Abnormalities | VALCYTE Tablets (N=370) %
Neutropenia: ANC/µL
< 500 | 19
500 – < 750 | 17
750 – < 1000 | 17
Anemia: Hemoglobin g/dL
< 6.5 | 7
6.5 – < 8.0 | 13
8.0 – < 9.5 | 16
Thrombocytopenia: Platelets/µL
< 25000 | 4
25000 – < 50000 | 6
50000 – < 100000 | 22
Serum Creatinine: mg/dL
> 2.5 | 3
> 1.5 – 2.5 | 12

Prevention of CMV Disease in Solid Organ Transplant Patients: Table 5 shows selected adverse reactions regardless of severity with an incidence of greater than or equal to 5% from a clinical trial (up to 28 days after study treatment) where heart, kidney, kidney-pancreas and liver transplant patients received VALCYTE tablets (N=244) or oral ganciclovir (N=126) until Day 100 post-transplant. The majority of the adverse reactions were of mild or moderate intensity.

Table 5 Percentage of Selected Grades 1–4 Adverse Reactions Reported in greater than or equal to 5% of Adult Patients From a Study of Solid Organ Transplant Patients
Adverse Reactions | VALCYTE Tablets (N=244) % | Oral Ganciclovir (N=126) %
Gastrointestinal disorders
Diarrhea | 30 | 29
Nausea | 23 | 23
Vomiting | 16 | 14
Nervous system disorders
Tremors | 28 | 25
Headache | 22 | 27
Insomnia | 20 | 16
General disorders and administration site conditions
Pyrexia | 13 | 14

Table 6 shows selected adverse reactions regardless of severity with an incidence of greater than or equal to 5% from another clinical trial where kidney transplant patients received either valganciclovir once daily starting within 10 days post-transplant until Day 100 post-transplant followed by 100 days of placebo or valganciclovir once daily until Day 200 post-transplant. The overall safety profile of VALCYTE did not change with the extension of prophylaxis until Day 200 post-transplant in high risk kidney transplant patients.

Table 6 Percentage of Selected Grades 1–4 Adverse Reactions Reported in greater than or equal to 5% of Adult Patients from a Study of Kidney Transplant Patients
Adverse Reactions | VALCYTE Tablets Day 100 Post-transplant (N=164) % | VALCYTE Tablets Day 200 Post-transplant (N=156) %
Gastrointestinal disorders
Diarrhea | 26 | 31
Nausea | 11 | 11
Vomiting | 3 | 6
Nervous system disorders
Tremors | 12 | 17
Headache | 10 | 6
Insomnia | 7 | 6
General disorders and administration site conditions
Pyrexia | 12 | 9

Table 7 and Table 8 show selected laboratory abnormalities reported with VALCYTE tablets in two trials in solid organ transplant patients.

Table 7 Selected Laboratory Abnormalities Reported in a Study of Adult Solid Organ Transplant Patients *
Laboratory Abnormalities | VALCYTE Tablets (N=244) % | Ganciclovir Capsules (N=126) %
Neutropenia: ANC/µL
< 500 | 5 | 3
500 – < 750 | 3 | 2
750 – < 1000 | 5 | 2
Anemia: Hemoglobin g/dL
< 6.5 | 1 | 2
6.5 – < 8.0 | 5 | 7
8.0 – < 9.5 | 31 | 25
Thrombocytopenia: Platelets/µL
< 25000 | 0 | 2
25000 – < 50000 | 1 | 3
50000 – < 100000 | 18 | 21
Serum Creatinine: mg/dL
> 2.5 | 14 | 21
> 1.5 – 2.5 | 45 | 47

Table 8 Selected Laboratory Abnormalities Reported in a Study of Adult Kidney Transplant Patients *
Laboratory Abnormalities | VALCYTE Tablets Day 100 Post-transplant (N=164) % | VALCYTE Tablets Day 200 Post-transplant (N=156) %
Neutropenia: ANC/µL
< 500 | 9 | 10
500 – < 750 | 6 | 6
750 – < 1000 | 7 | 5
Anemia: Hemoglobin g/dL
< 6.5 | 0 | 1
6.5 – < 8.0 | 5 | 1
8.0 – < 9.5 | 17 | 15
Thrombocytopenia: Platelets/µL
< 25000 | 0 | 0
25000 – < 50000 | 1 | 0
50000 – < 100000 | 7 | 3
Serum Creatinine: mg/dL
> 2.5 | 17 | 14
> 1.5 – 2.5 | 50 | 48

Other adverse drug reactions from VALCYTE in clinical trials in CMV retinitis and solid organ transplant patients

Other adverse drug reactions with VALCYTE in clinical trials in either patients with CMV retinitis or solid organ transplant patients that occurred in at least 5% of patients are listed below.

Eye disorders: retinal detachment, eye pain

Gastrointestinal disorders: dyspepsia, constipation, abdominal distention, mouth ulceration

General disorders and administration site conditions: fatigue, pain, malaise, asthenia, chills, peripheral edema

Hepatobiliary disorders: hepatic function abnormal

Infections and infestations: candida infections including oral candidiasis, upper respiratory tract infection, influenza, urinary tract infection, pharyngitis/nasopharyngitis, postoperative wound infection

Injury, poisoning, and procedural complications: postoperative complications, wound secretion

Metabolic and nutrition disorders: decreased appetite, hyperkalemia, hypophosphatemia, weight decreased

Musculoskeletal and connective tissue disorders: back pain, myalgia, arthralgia, muscle spasms

Nervous system disorders: insomnia, neuropathy peripheral, dizziness

Psychiatric disorders: depression, anxiety

Renal and urinary disorders: renal impairment, creatinine clearance renal decreased, blood creatinine increased, hematuria

Respiratory, thoracic and mediastinal disorders: cough, dyspnea

Skin and subcutaneous tissues disorders: dermatitis, night sweats, pruritus

Vascular disorders: hypotension

Other adverse reactions with VALCYTE in clinical trials in either patients with CMV retinitis or solid organ transplant patients that occurred in less than 5% of patients are listed below.

Blood and lymphatic disorders: febrile neutropenia, pancytopenia, bone marrow failure (including aplastic anemia)

Cardiovascular disorders: arrhythmia

Ear and labyrinth disorders: deafness

Eye disorders: macular edema

Gastrointestinal disorders: pancreatitis

Hemorrhage: potentially life-threatening bleeding associated with thrombocytopenia

Immune system disorders: hypersensitivity

Infections and infestations: cellulitis, sepsis

Injury, poisoning, and procedural complications: postoperative pain, wound dehiscence

Investigations: aspartate aminotransferase increased, alanine aminotransferase increased

Musculoskeletal and connective tissue disorders: limb pain

Nervous system disorders: seizure, dysguesia (taste disturbance)

Psychiatric disorders: confusional state, agitation, psychotic disorder, hallucinations

Renal and urinary disorders: renal failure

Adverse Reactions in Pediatric Patients:

VALCYTE for oral solution and tablets have been studied in 179 pediatric solid organ transplant patients who were at risk for developing CMV disease (aged 3 weeks to 16 years) and in 24 neonates with symptomatic congenital CMV disease (aged 8 to 34 days), with duration of ganciclovir exposure ranging from 2 to 200 days [see Use in Specific Populations (8.4), Clinical Studies (14.2)].

Prevention of CMV Disease in Pediatric Solid Organ Transplant Patients: The most frequently reported adverse reactions (greater than 10% of patients), regardless of seriousness, in pediatric solid organ transplant patients taking VALCYTE until Day 100 post-transplant were diarrhea, pyrexia, upper respiratory tract infection, vomiting, anemia, neutropenia, constipation and nausea. The most frequently reported adverse reactions (greater than 10% of patients) in pediatric kidney transplant patients treated with valganciclovir until Day 200 post-transplant were upper respiratory tract infection, urinary tract infection, diarrhea, leukopenia, neutropenia, headache, abdominal pain, tremor, pyrexia, anemia, blood creatinine increased, vomiting, and hematuria.

In general, the safety profile was similar in pediatric patients compared to that observed in adult patients. However, the rates of certain adverse reactions, and laboratory abnormalities, such as upper respiratory tract infection, pyrexia, nasopharyngitis, anemia, and abdominal pain were reported more frequently in pediatric patients than in adults [see Use in Specific Populations (8.4), Clinical Studies (14.2)]. Neutropenia was reported at a higher incidence in the two pediatric studies as compared to adults, but there was no correlation between neutropenia and infections observed in the pediatric population.

The overall safety profile of VALCYTE was similar with the extension of prophylaxis until Day 200 post-transplant in high risk pediatric kidney transplant patients. However, the incidence of severe neutropenia (ANC < 500/µL) was higher in pediatric kidney transplant patients treated with VALCYTE until Day 200 (17/57, 30%) compared to pediatric kidney transplant patients treated until Day 100 (3/63, 5%). There were no differences in the incidence of severe (Grade 4) anemia or thrombocytopenia in patients treated 100 or 200 days with VALCYTE.

6.2 Postmarketing Experience

The following adverse reactions have been identified during post-approval use of VALCYTE. Because these reactions are reported voluntarily from a population of uncertain size, it is not always possible to reliably estimate their frequency or establish a causal relationship to drug exposure. As VALCYTE is rapidly and extensively converted to ganciclovir, any adverse reactions associated with ganciclovir might also occur with valganciclovir.

- Anaphylactic reaction
- Agranulocytosis
- Granulocytopenia

In general, the adverse reactions reported during the postmarketing use of VALCYTE were similar to those identified during the clinical trials.

7 DRUG INTERACTIONS

In vivo drug-drug interaction studies were not conducted with valganciclovir. However, because valganciclovir is rapidly and extensively converted to ganciclovir, drug-drug interactions associated with ganciclovir will be expected for VALCYTE. Drug-drug interaction studies with ganciclovir were conducted in patients with normal renal function. Following concomitant administration of VALCYTE and other renally excreted drugs, patients with impaired renal function may have increased concentrations of ganciclovir and the coadministered drug. Therefore, these patients should be closely monitored for toxicity of ganciclovir and the coadministered drug.

Established and other potentially significant drug interactions conducted with ganciclovir are listed in Table 9.

Table 9 Established and Other Potentially Significant Drug Interactions with Ganciclovir
Name of the Concomitant Drug | Change in the Concentration of Ganciclovir or Concomitant Drug | Clinical Comment
Imipenem-cilastatin | Unknown | Coadministration with imipenem-cilastatin is not recommended because generalized seizures have been reported in patients who received ganciclovir and imipenem-cilastatin.
Cyclosporine or amphotericin B | Unknown | Monitor renal function when VALCYTE is coadministered with cyclosporine or amphotericin B because of potential increase in serum creatinine [see Warnings and Precautions (5.2)].
Mycophenolate mofetil (MMF) | ↔ Ganciclovir (in patients with normal renal function) ↔ MMF (in patients with normal renal function) | Based on increased risk, patients should be monitored for hematological and renal toxicity.
Other drugs associated with myelosuppression or nephrotoxicity (e.g., adriamycin, dapsone, doxorubicin, flucytosine, hydroxyurea, pentamidine, tacrolimus, trimethoprim/ sulfamethoxazole, vinblastine, vincristine, and zidovudine) | Unknown | Because of potential for higher toxicity, coadministration with VALCYTE should be considered only if the potential benefits are judged to outweigh the risks.
Didanosine | ↔ Ganciclovir ↑ Didanosine | Patients should be closely monitored for didanosine toxicity (e.g., pancreatitis)
Probenecid | ↑ Ganciclovir | VALCYTE dose may need to be reduced. Monitor for evidence of ganciclovir toxicity.

8 USE IN SPECIFIC POPULATIONS

8.1 Pregnancy

Risk Summary

After oral administration, valganciclovir (prodrug) is converted to ganciclovir (active drug) and, therefore, VALCYTE is expected to have reproductive toxicity effects similar to ganciclovir. In animal studies, ganciclovir caused maternal and fetal toxicity and embryo-fetal mortality in pregnant mice and rabbits as well as teratogenicity in rabbits at exposures two-times the human exposure. There are no available human data on use of VALCYTE or ganciclovir in pregnant women to establish the presence or absence of drug-associated risk. The background risk of major birth defects and miscarriage for the indicated populations is unknown. However, the background risk in the U.S. general population of major birth defects is 2–4% and the risk of miscarriage is 15–20% of clinically recognized pregnancies. Advise pregnant women of the potential risk to the fetus [see Warnings and Precautions (5.3), Use in Specific Populations (8.3)].

Clinical Considerations

Disease-associated maternal and/or embryo/fetal risk

Most maternal CMV infections are asymptomatic or they may be associated with a self-limited mononucleosis-like syndrome. However, in immunocompromised patients (i.e., transplant patients or patients with AIDS) CMV infections may be symptomatic and may result in significant maternal morbidity and mortality. The transmission of CMV to the fetus is a result of maternal viremia and transplacental infection. Perinatal infection can also occur from exposure of the neonate to CMV shedding in the genital tract. Approximately 10% of children with congenital CMV infection are symptomatic at birth. Mortality in these infants is about 10% and approximately 50–90% of symptomatic surviving newborns experience significant morbidity, including mental retardation, sensorineural hearing loss, microcephaly, seizures, and other medical problems. The risk of congenital CMV infection resulting from primary maternal CMV infection may be higher and of greater severity than that resulting from maternal reactivation of CMV infection.

Data

Animal Data

Doses resulting in two-times the human exposure of ganciclovir (based on the human AUC following a single intravenous infusion of 5 mg per kg of ganciclovir) resulted in maternal and embryo-fetal toxicity in pregnant mice and rabbits as well as teratogenicity in the rabbits. Fetal resorptions were present in at least 85% of rabbits and mice. Rabbits showed increased embryo-fetal mortality, growth retardation of the fetuses and structural abnormalities of multiple organs of the fetuses including the palate (cleft palate), eyes (anophthalmia/microphthalmia), brain (hydrocephalus), jaw (brachygnathia), kidneys and pancreas (aplastic organs). Increased embryo-fetal mortality was also seen in mice. Daily intravenous doses of approximately 1.7 times the human exposure (based on AUC) administered to female mice prior to mating, during gestation, and during lactation caused hypoplasia of the testes and seminal vesicles in the male offspring, as well as pathologic changes in the nonglandular region of the stomach.

Data from an ex-vivo human placental model showed that ganciclovir crosses the human placenta. The transfer occurred by passive diffusion and was not saturable over a concentration range of 1 to 10 mg/mL.

8.2 Lactation

Risk Summary

No data are available regarding the presence of valganciclovir (prodrug) or ganciclovir (active drug) in human milk, the effects on the breastfed infant, or the effects on milk production. Animal data indicate that ganciclovir is excreted in the milk of lactating rats. The Centers for Disease Control and Prevention recommend that HIV-infected mothers not breastfeed their infants to avoid risking postnatal transmission of HIV. Advise nursing mothers that breastfeeding is not recommended during treatment with VALCYTE because of the potential for serious adverse events in nursing infants and because of the potential for transmission of HIV [see Boxed Warning, Warnings and Precautions (5.1, 5.3, 5.4, 5.5), Nonclinical Toxicology (13.1)].

8.3 Females and Males of Reproductive Potential

Pregnancy Testing

Females of reproductive potential should undergo pregnancy testing before initiation of VALCYTE [see Use in Specific Populations (8.1)].

Contraception

Females

Because of the mutagenic and teratogenic potential of VALCYTE, females of reproductive potential should be advised to use effective contraception during treatment and for at least 30 days following treatment with VALCYTE [see Dosage and Administration (2.6), Warnings and Precautions (5.4, 5.5), Nonclinical Toxicology (13.1)].

Males

Because of its mutagenic potential, males should be advised to use condoms during and for at least 90 days following, treatment with VALCYTE [see Dosage and Administration (2.6), Warnings and Precautions (5.3, 5.5), Nonclinical Toxicology (13.1)].

Infertility

VALCYTE at the recommended doses may cause temporary or permanent female and male infertility [see Warnings and Precautions (5.3), Nonclinical Toxicology (13.1)].

Data

Human Data

In a small, open-label, non-randomized clinical study, adult male renal transplant patients receiving VALCYTE for CMV prophylaxis for up to 200 days post-transplantation were compared to an untreated control group. Patients were followed-up for six months after VALCYTE discontinuation. Among 24 evaluable patients in the VALCYTE group, the mean sperm density at the end of treatment visit decreased by 11 million/mL from baseline; whereas, among 14 evaluable patients in the control group the mean sperm density increased by 33 million/mL. However, at the follow-up visit among 20 evaluable patients in the VALCYTE group the mean sperm density was comparable to that observed among 10 evaluable patients in the untreated control group (the mean sperm density at the end of follow-up visit increased by 41 million/mL from baseline in the VALCYTE group and by 43 million/mL in the untreated group).

8.4 Pediatric Use

VALCYTE for oral solution and tablets are indicated for the prevention of CMV disease in pediatric kidney transplant patients 4 months to 16 years of age and in pediatric heart transplant patients 1 month to 16 years of age at risk for developing CMV disease [see Indications and Usage (1.2), Dosage and Administration (2.3)].

The use of VALCYTE for oral solution and tablets for the prevention of CMV disease in pediatric kidney transplant patients 4 months to 16 years of age is based on two single-arm, open-label, non-comparative studies in patients 4 months to 16 years of age. Study 1 was a safety and pharmacokinetic study in pediatric solid organ transplant patients (kidney, liver, heart, and kidney/pancreas). VALCYTE was administered once daily within 10 days of transplantation for a maximum of 100 days post-transplantation. Study 2 was a safety and tolerability study where VALCYTE was administered once daily within 10 days of transplantation for a maximum of 200 days post-transplantation in pediatric kidney transplant patients. The results of these studies were supported by previous demonstration of efficacy in adult patients [see Adverse Reactions (6.1), Clinical Pharmacology (12.3), Clinical Studies (14.2)].

The use of VALCYTE for oral solution and tablets for the prevention of CMV disease in pediatric heart transplant patients 1 month to 16 years of age is based on two studies (Study 1 described above and Study 3) and was supported by previous demonstration of efficacy in adult patients [see Clinical Pharmacology (12.3), Clinical Studies (14.2)]. Study 3 was a pharmacokinetic and safety study of VALCYTE in pediatric heart transplant patients less than 4 months of age who received a single dose of VALCYTE oral solution on each of two consecutive days. A physiologically based pharmacokinetic (PBPK) model was developed based on the available pharmacokinetic data from pediatric and adult patients to support dosing in heart transplant patients less than 1 month of age. However, due to uncertainty in model predictions for neonates, VALCYTE is not indicated for prophylaxis in this age group.

The safety and efficacy of VALCYTE for oral solution and tablets have not been established in children for prevention of CMV disease in pediatric liver transplant patients, in kidney transplant patients less than 4 months of age, in heart transplant patients less than 1 month of age, in pediatric AIDS patients with CMV retinitis, and in infants with congenital CMV infection.

A pharmacokinetic and pharmacodynamic evaluation of VALCYTE for oral solution was performed in 24 neonates with congenital CMV infection involving the central nervous system. All patients were treated for 6 weeks with a combination of intravenous ganciclovir 6 mg per kg twice daily or VALCYTE for oral solution at doses ranging from 14 mg per kg to 20 mg per kg twice daily. The pharmacokinetic results showed that in infants greater than 7 days to 3 months of age, a dose of 16 mg per kg twice daily of VALCYTE for oral solution provided ganciclovir systemic exposures (median AUC0-12h=23.6 [range 16.8–35.5] mcg∙h/mL; n=6) comparable to those obtained in infants up to 3 months of age from a 6 mg per kg dose of intravenous ganciclovir twice daily (AUC0-12h=25.3 [range 2.4–89.7] mcg∙h/mL; n=18) or to the ganciclovir systemic exposures obtained in adults from a 900 mg dose of VALCYTE tablets twice daily. However, the efficacy and safety of intravenous ganciclovir and of VALCYTE have not been established for the treatment of congenital CMV infection in infants and no similar disease occurs in adults; therefore, efficacy cannot be extrapolated from intravenous ganciclovir use in adults.

8.5 Geriatric Use

Studies of VALCYTE for oral solution or tablets have not been conducted in adults older than 65 years of age. Clinical studies of VALCYTE did not include sufficient numbers of subjects aged 65 and over to determine whether they respond differently from younger subjects. In general, dose selection for an elderly patient should be cautious, usually starting at the low end of the dosing range, reflecting the greater frequency of decreased hepatic, renal, or cardiac function, and of concomitant disease or other drug therapy. VALCYTE is known to be substantially excreted by the kidneys, and the risk of toxic reactions to this drug may be greater in patients with impaired renal function. Because renal clearance decreases with age, VALCYTE should be administered with consideration of their renal status. Renal function should be monitored and dosage adjustments should be made accordingly [see Dosage and Administration (2.5), Warnings and Precautions (5.2), Use in Specific Populations (8.6), Clinical Pharmacology (12.3)].

8.6 Renal Impairment

Dose reduction is recommended when administering VALCYTE to patients with renal impairment [see Dosage and Administration (2.5), Warnings and Precautions (5.2), Clinical Pharmacology (12.3)].

For adult patients on hemodialysis (CrCl less than 10 mL/min), VALCYTE tablets should not be used. Adult hemodialysis patients should use ganciclovir in accordance with the dose-reduction algorithm cited in the CYTOVENE®-IV complete product information section on DOSAGE AND ADMINISTRATION: Renal Impairment [see Dosage and Administration (2.5) and Clinical Pharmacology (12.3)].

8.7 Hepatic Impairment

The safety and efficacy of VALCYTE have not been studied in patients with hepatic impairment.

10 OVERDOSAGE

Experience with VALCYTE Tablets: An overdose of VALCYTE could possibly result in increased renal toxicity [see Dosage and Administration (2.5), Use in Specific Populations (8.6)]. Because ganciclovir is dialyzable, dialysis may be useful in reducing serum concentrations in patients who have received an overdose of VALCYTE [see Clinical Pharmacology (12.3)]. Adequate hydration should be maintained. The use of hematopoietic growth factors should be considered [see Warnings and Precautions (5.1) and Clinical Pharmacology (12.3)].

Reports of adverse reactions after overdoses with valganciclovir, some with fatal outcomes, have been received from clinical trials and during postmarketing experience. The majority of patients experienced one or more of the following adverse events:

Hematological toxicity: myelosuppression including pancytopenia, bone marrow failure, leukopenia, neutropenia, granulocytopenia

Hepatotoxicity: hepatitis, liver function disorder

Renal toxicity: worsening of hematuria in a patient with pre-existing renal impairment, acute kidney injury, elevated creatinine

Gastrointestinal toxicity: abdominal pain, diarrhea, vomiting

Neurotoxicity: generalized tremor, seizure

11 DESCRIPTION

VALCYTE contains valganciclovir hydrochloride (valganciclovir HCl), a hydrochloride salt of the L-valyl ester of ganciclovir that exists as a mixture of two diastereomers. Ganciclovir is a synthetic guanine derivative active against CMV.

VALCYTE is available as a 450 mg tablet for oral administration. Each tablet contains 496.3 mg of valganciclovir HCl (corresponding to 450 mg of valganciclovir), and the inactive ingredients microcrystalline cellulose, povidone K-30, crospovidone and stearic acid. The film-coat applied to the tablets contains Opadry Pink®.

VALCYTE is also available as a powder for oral solution, which when constituted with water as directed contains 50 mg/mL valganciclovir free base. The inactive ingredients of VALCYTE for oral solution are sodium benzoate, fumaric acid, povidone K-30, sodium saccharin, mannitol and tutti-frutti flavoring.

Valganciclovir HCl is a white to off-white crystalline powder with a molecular formula of C14H22N6O5∙HCl and a molecular weight of 390.83. The chemical name for valganciclovir HCl is L-Valine, 2-[(2-amino-1,6-dihydro-6-oxo-9H-purin-9-yl) methoxy]-3-hydroxypropyl ester, monohydrochloride. Valganciclovir HCl is a polar hydrophilic compound with a solubility of 70 mg/mL in water at 25°C at a pH of 7.0 and an n-octanol/water partition coefficient of 0.0095 at pH 7.0. The pKa for valganciclovir HCl is 7.6.

The chemical structure of valganciclovir HCl is:

All doses in this insert are specified in terms of valganciclovir.

12 CLINICAL PHARMACOLOGY

12.1 Mechanism of Action

Valganciclovir is an antiviral drug with activity against CMV [see Microbiology (12.4)].

12.3 Pharmacokinetics

Valganciclovir is a prodrug of ganciclovir. Valganciclovir Cmax and AUC are approximately 1% and 3% of those of ganciclovir, respectively.

Pharmacokinetics in Adults: The pharmacokinetics of ganciclovir after administration of valganciclovir tablets have been evaluated in HIV- and CMV-seropositive patients, patients with AIDS and CMV retinitis, and in solid organ transplant patients (Table 10).

Table 10 Ganciclovir Pharmacokinetics [Data were obtained from single and multiple dose studies in healthy volunteers, HIV-positive patients, and HIV-positive/CMV-positive patients with and without retinitis. Patients with CMV retinitis tended to have higher ganciclovir plasma concentrations than patients without CMV retinitis.] in Healthy Volunteers and HIV-positive/CMV-positive Adults Administered VALCYTE Tablets 900 mg Once Daily with Food
PK parameter | N | Value (Mean ± SD)
AUC0-24h (mcg∙h/mL) | 57 | 29.1 ± 9.7
Cmax (mcg/mL) | 58 | 5.61 ± 1.52
Absolute oral bioavailability (%) | 32 | 59.4 ± 6.1
Elimination half-life (hr) | 73 | 4.08 ± 0.76
Renal clearance (mL/min/kg) | 20 | 3.21 ± 0.75 (1 study, n=20)

The systemic ganciclovir exposures attained following administration of 900 mg VALCYTE tablets once daily were comparable across kidney, heart and liver transplant recipients (Table 11).

Table 11 Ganciclovir Pharmacokinetics in Solid Organ Transplant Recipients Administered VALCYTE Tablets 900 mg Once Daily with Food
Parameter | Value (Mean ± SD)
Parameter | Heart Transplant Recipients (N=17) | Liver Transplant Recipients (N=75) | Kidney Transplant Recipients [Includes kidney-pancreas] (N=68)
AUC0-24h (mcg∙h/mL) | 40.2 ± 11.8 | 46.0 ± 16.1 | 48.2 ± 14.6
Cmax (mcg/mL) | 4.9 ± 1.1 | 5.4 ± 1.5 | 5.3 ± 1.5
Elimination half-life (hr) | 6.58 ± 1.50 | 6.18 ± 1.42 | 6.77 ± 1.25

The pharmacokinetic parameters of ganciclovir following 200 days of VALCYTE administration in high-risk kidney transplant patients were similar to those in solid organ transplant patients who received VALCYTE for 100 days.

Absorption, Distribution, Metabolism, and Excretion

The pharmacokinetic (PK) properties of VALCYTE are provided in Table 12.

Table 12 Pharmacokinetic Properties of Ganciclovir and Valganciclovir Associated with VALCYTE
 | Valganciclovir | Ganciclovir
Absorption
Tmax (h) median (min-max) (fed conditions) |  | 2.18 1.7h to 3.0h
Food effect (high fat meal/fasting): PK parameter ratio and 90% confidence interval [Steady state ganciclovir PK was assessed after administration of VALCYTE tablets (875 mg once daily) with a high fat meal containing approximately 600 total calories (31.1 g fat, 51.6 g carbohydrates and 22.2 g protein) to 16 HIV-positive subjects.] |  | Cmax: 1.14 (0.95, 1.36) AUC: 1.30 (1.07, 1.51) Tmax: ↔
Distribution
% Bound to human plasma proteins (ex vivo) | Unknown | 1–2% over 0.5– 51 mcg/mL
Cerebrospinal fluid penetration | Unknown | Yes
Metabolism
 | Hydrolyzed by intestinal and liver esterases | No significant metabolism
Elimination
Dose proportionality |  | AUC was dose proportional under fed conditions across a valganciclovir dose range of 450 to 2625 mg
Major route of elimination | Metabolism to ganciclovir | Glomerular filtration and active tubular secretion
t1/2 (h) |  | See Tables 10 and 11
% Of dose excreted in urine | Unknown
% Of dose excreted in feces | Unknown

Specific Populations:

Renal Impairment: The pharmacokinetics of ganciclovir from a single oral dose of 900 mg VALCYTE tablets were evaluated in 24 otherwise healthy individuals with renal impairment. Decreased renal function results in decreased clearance of ganciclovir and increased terminal half-life (Table 13).

Table 13 Pharmacokinetics of Ganciclovir from a Single Oral Dose of 900 mg VALCYTE Tablets
Estimated Creatinine Clearance [Creatinine clearance calculated from 24-hour urine collection.] (mL/min) | N | Apparent Clearance (mL/min) Mean ± SD | AUClast (mcg∙h/mL) Mean ± SD | Half-life (hours) Mean ± SD
51-70 | 6 | 249 ± 99 | 49.5 ± 22.4 | 4.85 ± 1.4
21-50 | 6 | 136 ± 64 | 91.9 ± 43.9 | 10.2 ± 4.4
11-20 | 6 | 45 ± 11 | 223 ± 46 | 21.8 ± 5.2
≤ 10 | 6 | 12.8 ± 8 | 366 ± 66 | 67.5 ± 34

Hemodialysis reduces plasma concentrations of ganciclovir by about 50% following VALCYTE administration. Adult patients receiving hemodialysis (CrCl less than 10 mL/min) cannot use VALCYTE tablets because the daily dose of VALCYTE tablets required for these patients is less than 450 mg [see Dosage and Administration (2.5) and Use in Specific Populations (8.6)].

Pharmacokinetics in Pediatric Patients: The pharmacokinetics of ganciclovir were evaluated following the administration of valganciclovir in 63 pediatric solid organ transplant patients aged 4 months to 16 years, and in 16 pediatric heart transplant patients less than 4 months of age. In these studies, patients received oral doses of valganciclovir (either VALCYTE for oral solution or tablets) to produce exposure equivalent to an adult 900 mg dose [see Dosage and Administration (2.3), Adverse Reactions (6.1), Use in Specific Populations (8.4), Clinical Studies (14.2)].

In studies using the pediatric valganciclovir dosing algorithm, the pharmacokinetics of ganciclovir were similar across organ types and age ranges (Table 14). Relative to adult transplant patients (Table 11), AUC values in pediatric patients were somewhat increased, but were within the range considered safe and effective in adults.

Table 14 Ganciclovir Pharmacokinetics by Age in Pediatric Solid Organ Transplant Patients Administered VALCYTE
Organ | PK Parameter mean (SD) | Age Group
Organ | PK Parameter mean (SD) | < 4 months | 4 months to ≤ 2 years | > 2 to < 12 years | ≥ 12 years
Heart (N=26) | N | 14 [Ages ranged from 26 to 124 days.] | 6 | 2 | 4
Heart (N=26) | AUC0-24h (mcg∙h/mL) | 66.3 (20.5) | 55.4 (22.8) | 59.6 (21.0) | 60.6 (25.0)
Heart (N=26) | Cmax (mcg/mL) | 10.8 (3.30) | 8.2 (2.5) | 12.5 (1.2) | 9.5 (3.3)
Heart (N=26) | t1/2 (h) | 3.5 (0.87) | 3.8 (1.7) | 2.8 (0.9) | 4.9 (0.8)
Kidney (N=31) | N | NA | 2 | 10 | 19
Kidney (N=31) | AUC0-24h (mcg∙h/mL) | NA | 67.6 (13.0) | 55.9 (12.1) | 47.8 (12.4)
Kidney (N=31) | Cmax (mcg/mL) | NA | 10.4 (0.4) | 8.7 (2.1) | 7.7 (2.1)
Kidney (N=31) | t1/2 (h) | NA | 4.5 (1.5) | 4.8 (1.0) | 6.0 (1.3)
Liver (N=17) | N | NA | 9 | 6 | 2
Liver (N=17) | AUC0-24h (mcg∙h/mL) | NA | 69.9 (37.0) | 59.4 (8.1) | 35.4 (2.8)
Liver (N=17) | Cmax (mcg/mL) | NA | 11.9 (3.7) | 9.5 (2.3) | 5.5 (1.1)
Liver (N=17) | t1/2 (h) | NA | 2.8 (1.5) | 3.8 (0.7) | 4.4 (0.2)
N=number of patients, NA=not applicable

Pharmacokinetics in Geriatric Patients: The pharmacokinetic characteristics of VALCYTE in elderly patients have not been established.

DRUG INTERACTIONS

Drug Interactions: In vivo drug-drug interaction studies were not conducted with valganciclovir. However, because valganciclovir is rapidly and extensively converted to ganciclovir, interactions associated with ganciclovir will be expected for VALCYTE [see Drug Interactions (7)].

Table 15 and Table 16 provide a listing of established drug interaction studies with ganciclovir. Table 15 provides the effects of coadministered drug on ganciclovir plasma pharmacokinetic parameters, whereas Table 16 provides the effects of ganciclovir on plasma pharmacokinetic parameters of coadministered drug.

Table 15 Results of Drug Interaction Studies with Ganciclovir: Effects of Coadministered Drug on Ganciclovir Pharmacokinetic Parameters
Coadministered Drug | Ganciclovir Dosage | N | Ganciclovir Pharmacokinetic (PK) Parameter
Mycophenolate mofetil (MMF) 1.5 g single dose | 5 mg/kg IV single dose | 12 | No effect on ganciclovir PK parameters observed (patients with normal renal function)
Trimethoprim 200 mg once daily | 1000 mg every 8 hours | 12 | No effect on ganciclovir PK parameters observed
Didanosine 200 mg every 12 hours simultaneously administered with ganciclovir | 5 mg/kg IV twice daily | 11 | No effect on ganciclovir PK parameters observed
Didanosine 200 mg every 12 hours simultaneously administered with ganciclovir | 5 mg/kg IV once daily | 11 | No effect on ganciclovir PK parameters observed
Probenecid 500 mg every 6 hours | 1000 mg every 8 hours | 10 | AUC ↑ 53 ± 91% (range: -14% to 299%) Ganciclovir renal clearance ↓ 22 ± 20% (range: -54% to -4%)

Table 16 Results of Drug Interaction Studies with Ganciclovir: Effects of Ganciclovir on Pharmacokinetic Parameters of Coadministered Drug
Coadministered Drug | Ganciclovir Dosage | N | Coadministered Drug Pharmacokinetic (PK) Parameter
Oral cyclosporine at therapeutic doses | 5 mg/kg infused over 1 hour every 12 hours | 93 | In a retrospective analysis of liver allograft recipients, there was no evidence of an effect on cyclosporine whole blood concentrations.
Mycophenolate mofetil (MMF) 1.5 g single dose | 5 mg/kg IV single dose | 12 | No PK interaction observed (patients with normal renal function)
Trimethoprim 200 mg once daily | 1000 mg every 8 hours | 12 | No effect on trimethoprim PK parameters observed
Didanosine 200 mg every 12 hours | 5 mg/kg IV twice daily | 11 | AUC0-12 ↑70 ± 40% (range: 3% to 121%) Cmax↑49 ± 48% (range: -28% to 125%)
Didanosine 200 mg every 12 hours | 5 mg/kg IV once daily | 11 | AUC0-12 ↑50 ± 26% (range: 22% to 110%) Cmax ↑36 ± 36% (range: -27% to 94%)

12.4 Microbiology

Mechanism of Action: Valganciclovir is an L-valyl ester (prodrug) of ganciclovir that exists as a mixture of two diastereomers. After oral administration, both diastereomers are rapidly converted to ganciclovir by intestinal and hepatic esterases. Ganciclovir is a synthetic analogue of 2'-deoxyguanosine, which inhibits replication of human CMV in cell culture and in vivo.

In CMV-infected cells, ganciclovir is initially phosphorylated to ganciclovir monophosphate by the viral protein kinase, pUL97. Further phosphorylation occurs by cellular kinases to produce ganciclovir triphosphate, which is then slowly metabolized intracellularly (half-life 18 hours). As the phosphorylation is largely dependent on the viral kinase, phosphorylation of ganciclovir occurs preferentially in virus-infected cells. The virustatic activity of ganciclovir is due to inhibition of the viral DNA polymerase, pUL54 by ganciclovir triphosphate.

Antiviral Activity: The quantitative relationship between the cell culture susceptibility of human herpes viruses to antivirals and clinical response to antiviral therapy has not been established, and virus sensitivity testing has not been standardized. Sensitivity test results, expressed as the concentration of drug required to inhibit the growth of virus in cell culture by 50% (EC50), vary greatly depending upon a number of factors including the assay used. Thus, the reported EC50 values of ganciclovir that inhibit human CMV replication in cell culture (laboratory and clinical isolates) have ranged from 0.08 to 22.94 µM (0.02 to 5.75 mcg/mL). The distribution and range in susceptibility observed in one assay evaluating 130 clinical isolates was 0 to 1 µM (35%), 1.1 to 2 µM (20%), 2.1 to 3 µM (27%), 3.1 to 4 µM (13%), 4.1 to 5 µM (5%), less than 5 µM (less than 1%). Ganciclovir inhibits mammalian cell proliferation (CC50) in cell culture at higher concentrations ranging from 40 to greater than 1,000 µM (10.21 to greater than 250 mcg/mL). Bone marrow-derived colony-forming cells are more sensitive [CC50 value = 2.7 to 12 µM (0.69 to 3.06 mcg/mL)].

Viral Resistance:

Cell culture: CMV isolates with reduced susceptibility to ganciclovir have been selected in cell culture. Growth of CMV strains in the presence of ganciclovir resulted in the selection of amino acid substitutions in the viral protein kinase pUL97 (M460I/V, L595S, G598D, and K599T) and the viral DNA polymerase pUL54 (D301N, N410K, F412V, P488R, L516R, C539R, L545S, F595I, V812L, P829S, L862F, D879G, and V946L).

In vivo: Viruses resistant to ganciclovir can arise after prolonged treatment or prophylaxis with valganciclovir by selection of substitutions in pUL97 and/or pUL54. Limited clinical data are available on the development of clinical resistance to ganciclovir and many pathways to resistance likely exist. In clinical isolates, seven canonical pUL97 substitutions, (M460V/I, H520Q, C592G, A594V, L595S, and C603W) are the most frequently reported ganciclovir resistance-associated substitutions. These and other substitutions less frequently reported in the literature, or observed in clinical trials, are listed in Table 17.

Table 17 Summary of Resistance-associated Amino Acid Substitutions Observed in the CMV of Patients Failing Ganciclovir Treatment or Prophylaxis
pUL97 | F342Y, K359E/Q, L405P, A440V, M460I/V/T/L, V466G/M, C480F, C518Y, H520Q, P521L, del 590-593, A591D/V, C592F/G, A594E/G/T/V/P, L595F/S/T/W, del 595, del 595-603, E596D/G/Y, K599E/M, del 600-601, del 597-600, del 601-603, C603W/R/S/Y, C607F/S/Y, I610T, A613V
pUL54 | E315D, N408D/K/S, F412C/L/S, D413A/E/N, L501F/I, T503I, K513E/N/R, D515E, L516W, I521T, P522A/L/S, V526L, C539G, L545S/W, Q578H/L, D588E/N, G629S, S695T, I726T/V, E756K, L773V, V781I, V787E/L, L802M, A809V, T813S, T821I, A834P, G841A/S, D879G, A972V, del 981-982, A987G
Note: Many additional pathways to ganciclovir resistance likely exist

The presence of known ganciclovir resistance-associated amino acid substitutions was evaluated in a study that extended valganciclovir CMV prophylaxis from 100 days to 200 days post-transplant in adult kidney transplant patients at high risk for CMV disease (D+/R-) [see Clinical Studies (14.1)]. Five subjects from the 100 day group and four subjects from the 200 day group meeting the resistance analysis criteria had known ganciclovir resistance-associated amino acid substitutions detected. In six subjects, the following resistance-associated amino acid substitutions were detected within pUL97: 100 day group: A440V, M460V, C592G; 200 day group: M460V, C603W. In three subjects, the following resistance-associated amino acid substitutions were detected within pUL54: 100 day group: E315D; 200 day group: E315D, P522S. Overall, the detection of known ganciclovir resistance-associated amino acid substitutions was observed more frequently in patients during prophylaxis therapy than after the completion of prophylaxis therapy (during therapy: 5/12 [42%] versus after therapy: 4/58 [7%]). The possibility of viral resistance should be considered in patients who show poor clinical response or experience persistent viral excretion during therapy.

Cross-Resistance: Cross-resistance has been reported for amino acid substitutions selected in cell culture by ganciclovir, cidofovir or foscarnet. In general, amino acid substitutions in pUL54 conferring cross-resistance to ganciclovir and cidofovir are located within the exonuclease domains and region V of the viral DNA polymerase. Whereas, amino acid substitutions conferring cross-resistance to foscarnet are diverse, but concentrate at and between regions II (codon 696–742) and III (codon 805–845). The amino acid substitutions that resulted in reduced susceptibility to ganciclovir and either cidofovir and/or foscarnet are summarized in Table 18.

Substitutions at amino acid positions pUL97 340–400 have been found to confer resistance to ganciclovir. Resistance data based on assays that do not include this region should be interpreted cautiously.

Table 18 Summary of pUL54 Amino Acid Substitutions with Cross-Resistance between Ganciclovir, Cidofovir, and/or Foscarnet
Cross-resistant to cidofovir | D301N, N408D/K, N410K, F412C/L/S/V, D413E/N, P488R, L501I, T503I, K513E/N, L516R/W, I521T, P522S/A, V526L, C539G/R, L545S/W, Q578H, D588N, I726T/V, E756K, L733V, V787E, V812L, T813S, A834P, G841A, del 981-982, A987G
Cross-resistant to foscarnet | F412C, Q578H/L, D588N, V715A/M, E756K, L733V, V776M, V781I, V787E/L, L802M, A809V, V812L, T813S, T821I, A834P, G841A/S, del 981-982

13 NONCLINICAL TOXICOLOGY

13.1 Carcinogenesis, Mutagenesis, Impairment of Fertility

Long-term carcinogenicity studies have not been conducted with VALCYTE. However, upon oral administration, valganciclovir is rapidly and extensively converted to ganciclovir. Therefore, like ganciclovir, valganciclovir is a potential carcinogen.

Ganciclovir was carcinogenic in the mouse at oral doses that produced exposures approximately 0.1× and 1.4×, respectively, the mean drug exposure in humans following the recommended intravenous dose of 5 mg/kg, based on area under the plasma concentration curve (AUC) comparisons. At the higher dose, there was a significant increase in the incidence of tumors of the preputial gland in males, forestomach (nonglandular mucosa) in males and females, and reproductive tissues (ovaries, uterus, mammary gland, clitoral gland and vagina) and liver in females. At the lower dose, a slightly increased incidence of tumors was noted in the preputial and harderian glands in males, forestomach in males and females, and liver in females. Ganciclovir should be considered a potential carcinogen in humans.

Valganciclovir increases mutations in mouse lymphoma cells. In the mouse micronucleus assay, valganciclovir was clastogenic. Valganciclovir was not mutagenic in the Ames Salmonella assay. Ganciclovir increased mutations in mouse lymphoma cells and DNA damage in human lymphocytes in vitro. In the mouse micronucleus assay, ganciclovir was clastogenic. Ganciclovir was not mutagenic in the Ames Salmonella assay.

Valganciclovir is converted to ganciclovir and therefore is expected to have similar reproductive toxicity effects as ganciclovir [see Warnings and Precautions (5.3)]. Ganciclovir caused decreased mating behavior, decreased fertility, and an increased incidence of embryolethality in female mice following intravenous doses that produced an exposure approximately 1.7× the mean drug exposure in humans following the dose of 5 mg per kg, based on AUC comparisons. Ganciclovir caused decreased fertility in male mice and hypospermatogenesis in mice and dogs following daily oral or intravenous administration. Systemic drug exposure (AUC) at the lowest dose showing toxicity in each species ranged from 0.03 to 0.1× the AUC of the recommended human intravenous dose. Valganciclovir caused similar effects on spermatogenesis in mice, rats, and dogs. These effects were reversible at lower doses but irreversible at higher doses. It is considered likely that ganciclovir (and valganciclovir) could cause temporary or permanent inhibition of human spermatogenesis.

14 CLINICAL STUDIES

14.1 Adult Patients

Induction Therapy of CMV Retinitis: In one randomized open-label controlled study, 160 patients with AIDS and newly diagnosed CMV retinitis were randomized to receive treatment with either VALCYTE tablets (900 mg twice daily for 21 days, then 900 mg once daily for 7 days) or with intravenous ganciclovir solution (5 mg per kg twice daily for 21 days, then 5 mg per kg once daily for 7 days). Study participants were: male (91%), White (53%), Hispanic (31%), and Black (11%). The median age was 39 years, the median baseline HIV-1 RNA was 4.9 log10, and the median CD4 cell count was 23 cells/mm^3. A determination of CMV retinitis progression by the masked review of retinal photographs taken at baseline and Week 4 was the primary outcome measurement of the 3-week induction therapy. Table 19 provides the outcomes at 4 weeks.

Table 19 Week 4 Masked Review of Retinal Photographs in CMV Retinitis Study
 | Intravenous Ganciclovir | VALCYTE Tablets
Determination of CMV retinitis progression at Week 4 | N=80 | N=80
Progressor | 7 | 7
Non-progressor | 63 | 64
Death | 2 | 1
Discontinuations due to Adverse Events | 1 | 2
Failed to return | 1 | 1
CMV not confirmed at baseline or no interpretable baseline photos | 6 | 5

Maintenance Therapy of CMV Retinitis: No comparative clinical data are available on the efficacy of VALCYTE tablets for the maintenance therapy of CMV retinitis because all patients in the CMV retinitis study received open-label VALCYTE tablets after Week 4. However, the AUC for ganciclovir is similar following administration of 900 mg VALCYTE tablets once daily and 5 mg per kg intravenous ganciclovir once daily. Although the ganciclovir Cmax is lower following VALCYTE tablets administration compared to intravenous ganciclovir, it is higher than the Cmax obtained following oral ganciclovir administration. Therefore, use of VALCYTE tablets as maintenance therapy is supported by a plasma concentration-time profile similar to that of two approved products for maintenance therapy of CMV retinitis.

Prevention of CMV Disease in Heart, Kidney, Kidney-Pancreas, or Liver Transplantation: A double blind, double-dummy active comparator study was conducted in 372 heart, liver, kidney, or kidney-pancreas transplant patients at high risk for CMV disease (D+/R-). Patients were randomized (2 VALCYTE: 1 oral ganciclovir) to receive either VALCYTE tablets (900 mg once daily) or oral ganciclovir (1000 mg three times a day) starting within 10 days of transplantation until Day 100 post-transplant. The proportion of patients who developed CMV disease, including CMV syndrome and/or tissue-invasive disease during the first 6 months post-transplant was similar between the VALCYTE tablets arm (12.1%, N=239) and the oral ganciclovir arm (15.2%, N=125). However, in liver transplant patients, the incidence of tissue-invasive CMV disease was significantly higher in the VALCYTE group compared with the ganciclovir group. These results are summarized in Table 20.

Mortality at six months was 3.7% (9/244) in the VALCYTE group and 1.6% (2/126) in the oral ganciclovir group.

Table 20 Percentage of Patients with CMV Disease, Tissue-Invasive CMV Disease or CMV Syndrome by Organ Type: Endpoint Committee, 6 Month ITT Population
 | CMV Disease [Number of patients with CMV disease = Number of patients with tissue-invasive CMV disease or CMV syndrome] |  | Tissue-Invasive CMV Disease |  | CMV Syndrome [CMV syndrome was defined as evidence of CMV viremia accompanied with fever greater than or equal to 38°C on two or more occasions separated by at least 24 hours within a 7-day period and one or more of the following: malaise, leukopenia, atypical lymphocytosis, thrombocytopenia, and elevation of hepatic transaminases]
Organ | VGCV (N=239) | GCV (N=125) | VGCV (N=239) | GCV (N=125) | VGCV (N=239) | GCV (N=125)
Liver (n=177) | 19% (22/118) | 12% (7/59) | 14% (16/118) | 3% (2/59) | 5% (6/118) | 8% (5/59)
Kidney (n=120) | 6% (5/81) | 23% (9/39) | 1% (1/81) | 5% (2/39) | 5% (4/81) | 18% (7/39)
Heart (n=56) | 6% (2/35) | 10% (2/21) | 0% (0/35) | 5% (1/21) | 6% (2/35) | 5% (1/21)
Kidney/Pancreas (n=11) | 0% (0/5) | 17% (1/6) | 0% (0/5) | 17% (1/6) | 0% (0/5) | 0% (0/6)
GCV = oral ganciclovir; VGCV = valganciclovir

Prevention of CMV Disease in Kidney Transplantation: A double-blind, placebo-controlled study was conducted in 326 kidney transplant patients at high risk for CMV disease (D+/R-) to assess the efficacy and safety of extending VALCYTE CMV prophylaxis from 100 to 200 days post-transplant. Patients were randomized (1:1) to receive VALCYTE tablets (900 mg once daily) within 10 days of transplantation either until Day 200 post-transplant or until Day 100 post-transplant followed by 100 days of placebo. Extending CMV prophylaxis with VALCYTE until Day 200 post-transplant demonstrated superiority in preventing CMV disease within the first 12 months post-transplant in high risk kidney transplant patients compared to the 100 day dosing regimen (primary endpoint). These results are summarized in Table 21.

Table 21 Percentage of Kidney Transplant Patients with CMV Disease, Tissue-Invasive CMV Disease or CMV Syndrome, 12 Month ITT Population
 | CMV Disease [Number of patients with CMV disease = Number of patients with tissue-invasive CMV disease or CMV syndrome] |  | Tissue-Invasive CMV Disease |  | CMV Syndrome [CMV syndrome was defined as evidence of CMV viremia accompanied with at least one of the following: fever (greater than or equal to 38°C), severe malaise, leukopenia, atypical lymphocytosis, thrombocytopenia, and elevation of hepatic transaminases]
 | 100 Days VGCV (N=163) | 200 Days VGCV (N=155) | 100 Days VGCV (N=163) | 200 Days VGCV (N=155) | 100 Days VGCV (N=163) | 200 Days VGCV (N=155)
Cases | 36.8% (60/163) | 16.8% (26/155) | 1.8% (3/163) [Two patients in the 100 day group had both tissue-invasive CMV disease and CMV syndrome; however, these patients are counted as having only tissue-invasive CMV disease.] | 0.6% (1/155) | 35. 0% (57/163) | 16.1% (25/155)
VGCV = valganciclovir.

The percentage of kidney transplant patients with CMV disease at 24 months post-transplant was 38.7% (63/163) for the 100 day dosing regimen and 21.3% (33/155) for the 200 day dosing regimen.

14.2 Pediatric Patients

Prevention of CMV in Pediatric Heart, Kidney, or Liver Transplantation: Sixty-three children, 4 months to 16 years of age, who had a solid organ transplant (kidney 33, liver 17, heart 12, and kidney/liver 1) and were at risk for developing CMV disease, were enrolled in an open-label, safety, and pharmacokinetic study of oral VALCYTE (VALCYTE for oral solution or tablets). Patients received VALCYTE once daily within 10 days after transplant until a maximum of 100 days post-transplant. The daily doses of VALCYTE were calculated at each study visit based on body surface area and a modified creatinine clearance [see Dosage and Administration (2.3)].

The pharmacokinetics of ganciclovir were similar across organ transplant types and age ranges. The mean daily ganciclovir exposures in pediatric patients were somewhat increased relative to those observed in adult solid organ transplant patients receiving VALCYTE 900 mg once daily, but were within the range considered safe and effective in adults [see Clinical Pharmacology (12.3)]. No case of CMV syndrome or tissue-invasive CMV disease was reported within the first six months post-transplantation.

Prevention of CMV in Pediatric Kidney Transplantation: Fifty-seven children, 1 to 16 years of age, who had a renal transplant and were at risk for developing CMV disease, were enrolled in an open-label tolerability study of oral VALCYTE (VALCYTE for oral solution or tablets). Patients received VALCYTE once daily within 10 days after transplant until a maximum of 200 days post-transplant. The daily doses of VALCYTE were calculated at each study visit based on body surface area and a modified creatinine clearance [see Dosage and Administration (2.3)]. No case of CMV syndrome or tissue-invasive CMV disease was reported within the first 12 months post-transplantation.

15 REFERENCES

1. Brion LP, Fleischman AR, McCarton C, Schwartz GJ. A simple estimate of glomerular filtration rate in low birth weight infants during the first year of life: noninvasive assessment of body composition and growth. J of Ped 1986: 109(4): 698-707.

2. NIOSH [2014]. NIOSH list of antineoplastic and other hazardous drugs in healthcare settings. By Connor TH, MacKenzie BA, DeBord DG, Trout DB, O'Callaghan JP, Cincinnati, OH: U.S. Department of Health and Human Services, Centers for Disease Control and Prevention, National Institute for Occupational Safety and Health, DHHS (NIOSH) Publication No. 2014-138 (Supersedes 2012-150).

16 HOW SUPPLIED/STORAGE AND HANDLING

VALCYTE tablets: Supplied as 450 mg, pink, convex oval tablets with "VGC" on one side and "450" on the other side. Each tablet contains 450 mg valganciclovir. VALCYTE is supplied in bottles of 60 tablets (NDC 61269-480-60).

STORAGE AND HANDLING

Store VALCYTE tablets at 20°C to 25°C (68°F to 77°F); excursions are permitted to 15°C to 30°C (59°F to 86°F) [see USP controlled room temperature].

VALCYTE for oral solution: Supplied as a white to slightly yellow powder blend for constitution, forming a colorless to brownish-yellow tutti-frutti flavored solution. Available in glass bottles containing approximately 100 mL of solution after constitution. Each bottle can deliver up to a total of 88 mL of solution. Each bottle is supplied with a bottle adapter and 2 oral dispensers (NDC 61269-485-10).

Prior to dispensing to the patient, VALCYTE for oral solution must be prepared by the pharmacist [see Dosage and Administration (2.4)].

STORAGE AND HANDLING

Store dry powder at 20°C to 25°C (68°F to 77°F); excursions are permitted to 15°C to 30°C (59°F to 86°F) [see USP controlled room temperature].

Store constituted solution under refrigeration at 2°C to 8°C (36°F to 46°F) for no longer than 49 days. Do not freeze.

17 PATIENT COUNSELING INFORMATION

Advise the patient to read the FDA-approved patient labeling (Patient Information and Instructions for Use).

Serious Adverse Reactions

Inform patients that VALCYTE may cause granulocytopenia (neutropenia), anemia, thrombocytopenia and elevated creatinine levels and that dose modification or discontinuation of dosing may be required. Complete blood counts, platelet counts, and creatinine levels should be monitored frequently during treatment [see Warnings and Precautions (5.1)].

Pregnancy and Contraception

Inform females of reproductive potential that VALCYTE causes birth defects in animals. Advise them to use effective contraception during and for at least 30 days following treatment with VALCYTE. Similarly, advise males to use condoms during and for at least 90 days following treatment with VALCYTE [see Use in Specific Populations (8.1, 8.3)].

Carcinogenicity

Advise patients that VALCYTE is considered a potential carcinogen [see Nonclinical Toxicity (13.1)].

Lactation

Advise mothers not to breast-feed if they are receiving VALCYTE because of the potential for hematologic toxicity and cancer in nursing infants, and because HIV can be passed to the baby in breast milk [see Use in Specific Populations (8.2)].

Infertility

Advise patients that VALCYTE may cause temporary or permanent female and male infertility [see Warnings and Precautions (5.3), Use in Specific Populations (8.3)].

Impairment of Cognitive Ability

Inform patients that tasks requiring alertness may be affected including the patient's ability to drive and operate machinery as seizures, dizziness, and/or confusion have been reported with the use of VALCYTE [see Adverse Reactions (6.1)].

Use in Patients with CMV Retinitis

Inform patients that VALCYTE is not a cure for CMV retinitis, and they may continue to experience progression of retinitis during or following treatment. Advise patients to have ophthalmologic follow-up examinations at a minimum of every 4 to 6 weeks while being treated with VALCYTE. Some patients will require more frequent follow-up.

Administration

Inform adult patients that they should use VALCYTE tablets, not VALCYTE for oral solution [see Dosage and Administration (2.1)].

Inform patients to take VALCYTE with food to maximize bioavailability.

VALCYTE is a registered trademark of CHEPLAPHARM Arzneimittel GmbH.

Distributed by:
H2-Pharma, LLC
Montgomery, AL 36117, USA

Licensed by:
CHEPLAPHARM Arzneimittel GmbH
Ziegelhof 24, 17489 Greifswald, Germany

© 2023 CHEPLAPHARM Arzneimittel GmbH. All rights reserved.

For more information call 1-866-946-3684. © 2023 CHEPLAPHARM Arzneimittel GmbH. All rights reserved.

PATIENT INFORMATION

VALCYTE (Val-site)
(valganciclovir)
tablets

VALCYTE (Val-site)
(valganciclovir)
for oral solution

What is the most important information I should know about VALCYTE?
VALCYTE can cause serious side effects, including:

- Blood and bone marrow problems. VALCYTE can affect the bone marrow lowering the amount of your white blood cells, red blood cells, and platelets and may cause serious and life-threatening problems.
- Kidney failure. Kidney failure may happen in people who are elderly, people who take VALCYTE with certain other medicines, or people who are not adequately hydrated.
- Fertility problems. VALCYTE may lower sperm count in males and cause fertility problems. VALCYTE may also cause fertility problems in women. Talk to your healthcare provider if this is a concern for you.

- Birth defects. VALCYTE causes birth defects in animals. It is not known if VALCYTE causes birth defects in people. If you are a female who can become pregnant, you should use effective birth control during treatment with VALCYTE and for at least 30 days after treatment. If you are pregnant, talk to your healthcare provider before starting treatment with VALCYTE. If you are a female who can become pregnant, you should have a pregnancy test done before starting VALCYTE.
  - Tell your healthcare provider right away if you become pregnant during treatment with VALCYTE.
  - Males should use condoms during treatment with VALCYTE, and for at least 90 days after treatment, if their female sexual partner can become pregnant. Talk to your healthcare provider if you have questions about birth control.

- Cancer. VALCYTE causes cancer in animals and may potentially cause cancer in people.

Your healthcare provider will do regular blood tests during treatment with VALCYTE to check you for side effects. Your healthcare provider may change your dose or stop treatment with VALCYTE if you have serious side effects.

What is VALCYTE?
VALCYTE is a prescription antiviral medicine.
In adults, VALCYTE tablets are used:

- to treat cytomegalovirus (CMV) retinitis in people who have acquired immunodeficiency syndrome (AIDS). When CMV virus infects the eyes, it is called CMV retinitis. If CMV retinitis is not treated, it can cause blindness.
- to prevent CMV disease in people who have received a kidney, heart, or kidney-pancreas transplant and who have a high risk for getting CMV disease.

VALCYTE does not cure CMV retinitis. You may still get retinitis or worsening of retinitis during or after treatment with VALCYTE. It is important to stay under a healthcare provider's care and have your eyes checked at least every 4 to 6 weeks during treatment with VALCYTE.
In children, VALCYTE tablets or oral solution are used:

- to prevent CMV disease in children 4 months to 16 years of age who have received a kidney transplant and have a high risk for getting CMV disease.
- to prevent CMV disease in children 1 month to 16 years of age who have received a heart transplant and have a high risk for getting CMV disease.

It is not known if VALCTYE is safe and effective in children for prevention of CMV disease in liver transplant, in kidney transplant in infants less than 4 months of age, in heart transplant in infants less than 1 month of age, in children with AIDS who have CMV retinitis, and in infants with congenital CMV infection.

Do not take VALCYTE if you have had a serious allergic reaction to valganciclovir, ganciclovir or any of the ingredients of VALCYTE. See the end of this leaflet for a list of the ingredients in VALCYTE.

Before you take VALCYTE, tell your healthcare provider about all of your medical conditions, including if you:

- have low blood cell counts
- have kidney problems
- are receiving hemodialysis
- are receiving radiation treatment
- are pregnant or plan to become pregnant. See "What is the most important information I should know about VALCYTE?"
- are breastfeeding or plan to breastfeed. It is not known if VALCYTE passes into your breast milk. You should not breastfeed if you take VALCYTE.
  - You should not breastfeed if you have Human Immunodeficiency Virus (HIV-1) because of the risk of passing HIV-1 to your baby.
  - Talk to your healthcare provider about the best way to feed your baby.

Tell your healthcare provider about all the medicines you take,including prescription and over-the-counter medicines, vitamins and herbal supplements. VALCYTE and other medicines may affect each other and cause serious side effects. Keep a list of your medicines to show your healthcare provider and pharmacist.

- You can ask your healthcare provider or pharmacist for a list of medicines that interact with VALCYTE.
- Do not start taking a new medicine without telling your healthcare provider. Your healthcare provider can tell you if it is safe to take VALCYTE with other medicines.

How should I take VALCYTE?

- Take VALCYTE exactly as your healthcare provider tells you. Your dose of VALCYTE will depend on your medical condition.
- Adults should only take VALCYTE tablets. Children may take either VALCYTE tablets or oral solution.
- Take VALCYTE with food.
- Do not break or crush VALCYTE tablets. Avoid contact with your skin or eyes. If you come in contact with the contents of the tablet or oral solution, wash your skin well with soap and water or rinse your eyes well with plain water.
- If your child is prescribed VALCYTE for oral solution, your pharmacist will give you oral dosing dispensers to measure your child's dose of VALCYTE for oral solution. To be sure you receive the prescribed dose, it is important to use the dispenser provided to you. See the detailed Instructions for Use below for information about how to take VALCYTE for oral solution. Ask your pharmacist if you have any questions. If you lose or damage your oral dispensers and cannot use them, contact your pharmacist.
- If you take too much VALCYTE, call your healthcare provider or go to the nearest hospital emergency room right away.

What should I avoid during treatment with VALCYTE?
VALCYTE can cause seizures, dizziness, and confusion. You should not drive a car or operate machinery until you know how VALCYTE affects you.

What are the possible side effects of VALCYTE?
VALCYTE may cause serious side effects, including:
See "What is the most important information I should know about VALCYTE?"
The most common side effects of VALCYTE in adults include:

- diarrhea
- fever
- fatigue
- nausea
- shaky movements (tremors)

- low white cell, red cell and platelet cell counts in blood tests
- headache
- sleeplessness
- urinary tract infection
- vomiting

The most common side effects of VALCYTE in children include:

- diarrhea
- fever
- upper respiratory tract infection
- urinary tract infection

- vomiting
- low white blood cell counts in blood tests
- headache

These are not all the possible side effects of VALCYTE.
Call your doctor for medical advice about side effects. You may report side effects to FDA at 1-800-FDA-1088.

How should I store VALCYTE?

- Store VALCYTE tablets at room temperature between 68°F to 77°F (20°C to 25°C).
- Store VALCYTE for oral solution in the refrigerator between 36°F to 46°F (2°C to 8°C), for no longer than 49 days.
- Do not freeze.
- Do not keep VALCYTE that is out of date or that you no longer need.

Keep VALCYTE and all medicines out of the reach of children.

General information about the safe and effective use of VALCYTE.
Medicines are sometimes prescribed for purposes other than those listed in a Patient Information leaflet. Do not use VALCYTE for a condition for which it was not prescribed. Do not give VALCYTE to other people, even if they have the same symptoms you have. It may harm them. You can ask your pharmacist or healthcare provider for information about VALCYTE that is written for health professionals.

What are the ingredients in VALCYTE?
Active ingredient: valganciclovir hydrochloride
Inactive ingredients for tablets: microcrystalline cellulose, povidone K-30, crospovidone, and stearic acid. The film-coating applied to the tablets contains Opadry Pink®.
Inactive ingredients for oral solution: sodium benzoate, fumaric acid, povidone K-30, sodium saccharin, mannitol and tutti-frutti flavoring.

VALCYTE is a registered trademark of CHEPLAPHARM Arzneimittel GmbH.

Distributed by:
H2-Pharma, LLC
Montgomery, AL 36117, USA

Licensed by:
CHEPLAPHARM Arzneimittel GmbH
Ziegelhof 24, 17489 Greifswald, Germany

Revised: 04/2023

For more information call 1-866-946-3684.

© 2023 CHEPLAPHARM Arzneimittel GmbH. All rights reserved.

Instructions for Use VALCYTE (Val-site) (valganciclovir) for oral solution

Be sure that you read, and that you understand and follow these instructions carefully to ensure proper dosing of the oral solution.

Important:

- Avoid contact with your skin or eyes. If you come in contact with the contents of the oral solution, wash your skin well with soap and water or rinse your eyes well with plain water.
- Do not use VALCYTE for oral solution after the discard date on the bottle.
- Always use the oral dispenser provided to give or take a dose of VALCYTE for oral solution.
- Call your pharmacist if your oral dispenser is lost or damaged, and they will tell you how to continue to give or take a dose of VALCYTE for oral solution.
- Ask your healthcare provider or pharmacist to show you how to measure your prescribed dose.

To take a dose of VALCYTE for oral solution, you will need the bottle of medicine and an oral dispenser provided with the medicine (see Figure 1). Your pharmacist inserts the bottle adapter in the VALCYTE for oral solution bottle.

Figure 1

Step 1: With the child-resistant cap on the bottle, shake the bottle well for about 5 seconds before each use.

Step 2: Open the bottle by pressing downward firmly on the child-resistant cap and turning it counter-clockwise. Do not throw away the child-resistant cap.

Step 3: Check the dose in milliliters (mL) as prescribed by your healthcare provider. Find this number on the oral dispenser.

Step 4: Push the plunger down toward the tip of the oral dispenser.

Step 5: With the bottle in an upright position, insert the oral dispenser into the bottle adapter opening until firmly in place.

Step 6: Carefully turn the bottle upside down with the oral dispenser in place. Pull the plunger to withdraw the prescribed dose.
If you see air bubbles in the oral dispenser, fully push in the plunger so that the oral solution flows back into the bottle.
Then withdraw your prescribed dose of VALCYTE for oral solution.

Step 7: Leave the oral dispenser in the bottle adapter and turn the bottle to an upright position. Slowly remove the oral dispenser from the bottle adapter.

Step 8:Give or take the dose of VALCYTE for oral solution.

- Place the tip of the oral dispenser in the mouth.
- Slowly push down the oral dispenser plunger until the oral dispenser is empty.

Step 9: Put the child-resistant cap back on the bottle. Return the bottle back to the refrigerator.

Step 10: Rinse the oral dispenser with tap water after each use.

- Remove the plunger from the oral dispenser barrel by pulling the plunger all the way out of the barrel.
- Rinse the oral dispenser barrel and plunger with water and let them air dry.

- When the oral dispenser barrel and plunger are dry, put the plunger back into the oral dispenser barrel for the next use.

Do not throw away the oral dispenser.

How should I store VALCYTE for oral solution?

- Store solution in the refrigerator at 36°F to 46°F (2°C to 8°C) for no longer than 49 days.
- Do not freeze.

This Patient Information and Instructions for Use have been approved by the U.S. Food and Drug Administration.

VALCYTE is a registered trademark of CHEPLAPHARM Arzneimittel GmbH.

Distributed by:
H2-Pharma, LLC
Montgomery, AL 36117, USA

Licensed by:
CHEPLAPHARM Arzneimittel GmbH
Ziegelhof 24, 17489 Greifswald, Germany

Revised: 04/2023

For more information call 1-866-946-3684.

© 2023 CHEPLAPHARM Arzneimittel GmbH. All rights reserved.

Representative sample of labeling (see the HOW SUPPLIED section for complete listing):

PRINCIPAL DISPLAY PANEL - 450 mg Bottle Carton

NDC 61269-480-60

Valcyte®
(valganciclovir)
tablets

450 mg

DO NOT BREAK OR CRUSH TABLETS

CAUTION: Strict adherence to dosage
recommendations is essential to avoid
overdose.

60 tablets
Rx only

CHEPLAPHARM

PRINCIPAL DISPLAY PANEL - 100 mL Bottle Carton

NDC 61269-485-10

Valcyte®
(valganciclovir)
for oral solution

50 mg/mL

Each mL of constituted oral
solution contains 50 mg
valganciclovir free base.

100 mL (3.4 fl oz)

Rx only

CHEPLAPHARM